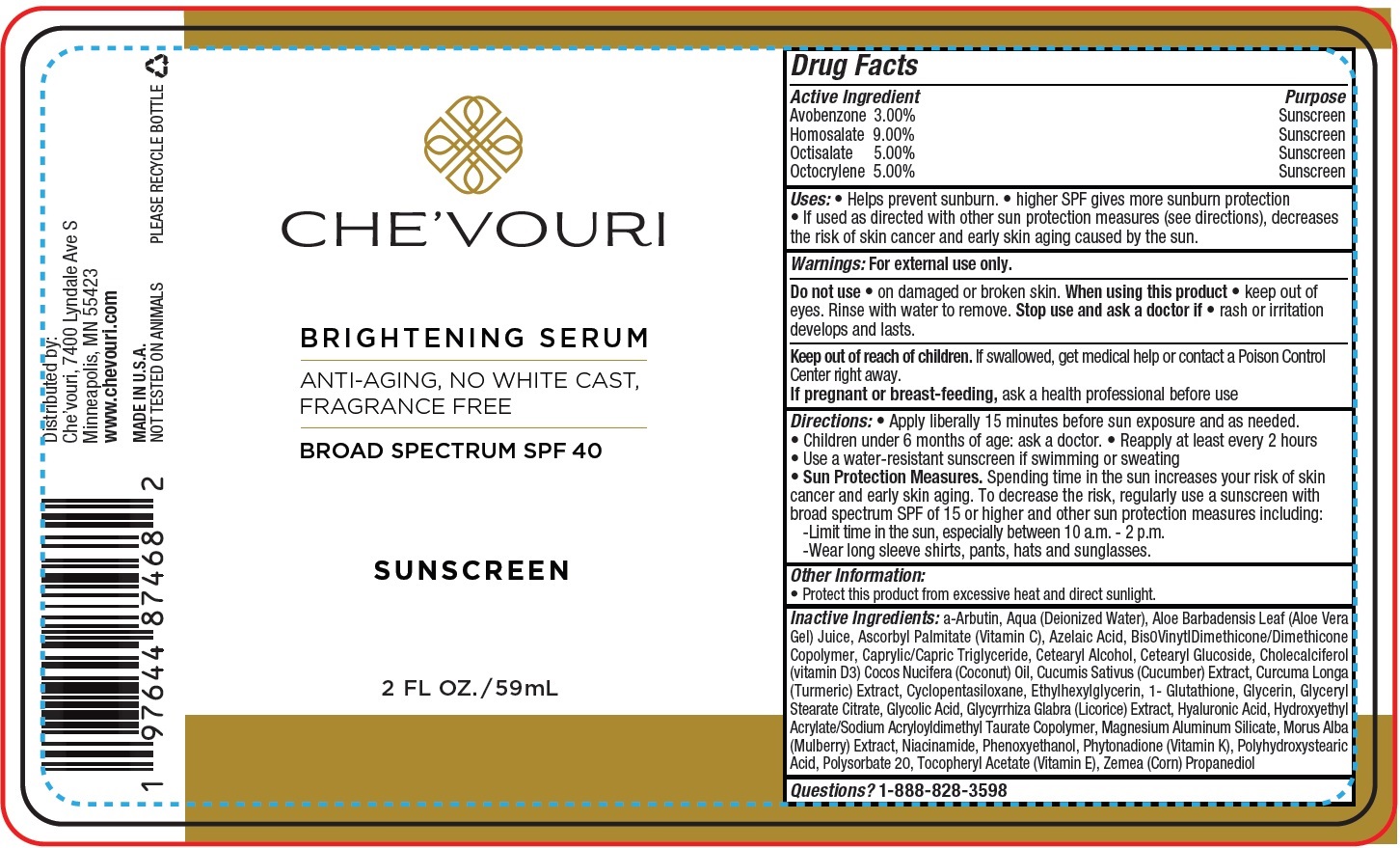 DRUG LABEL: CHEVOURI Brightening Serum Broad Spectrum SPF-40
NDC: 83880-440 | Form: CREAM
Manufacturer: CHE'VOURI LLC
Category: otc | Type: HUMAN OTC DRUG LABEL
Date: 20231218

ACTIVE INGREDIENTS: AVOBENZONE 30 mg/1 mL; HOMOSALATE 90 mg/1 mL; OCTISALATE 50 mg/1 mL; OCTOCRYLENE 50 mg/1 mL
INACTIVE INGREDIENTS: ALPHA-ARBUTIN; WATER; ALOE VERA LEAF; ASCORBYL PALMITATE; AZELAIC ACID; MEDIUM-CHAIN TRIGLYCERIDES; CETOSTEARYL ALCOHOL; CETEARYL GLUCOSIDE; CHOLECALCIFEROL; COCONUT OIL; CUCUMBER; TURMERIC; CYCLOMETHICONE 5; ETHYLHEXYLGLYCERIN; GLYCERIN; GLYCERYL STEARATE CITRATE; GLYCOLIC ACID; GLYCYRRHIZA GLABRA; HYALURONIC ACID; MAGNESIUM ALUMINUM SILICATE; WHITE MULBERRY; NIACINAMIDE; PHENOXYETHANOL; PHYTONADIONE; POLYSORBATE 20; .ALPHA.-TOCOPHEROL ACETATE; CORN

CHE'VOURI Brightening Serum Broad Spectrum SPF-40

Active Ingredient

Avobenzone 3.00%
Homosalate 9.00%
Octisalate 5.00%
Octocrylene 5.00%

Purpose

Sunscreen

Uses:

- Helps prevent sunburn.
- higher SPF gives more sunburn protection
- If used as directed with other sun protection measures (see directions), decreases the risk of skin cancer and early skin aging caused by the sun.

Warnings:

For external use only.

Do not use

- on damaged or broken skin.

When using this product

- keep out of eyes. Rinse with water to remove.

Stop use and ask a doctor if

- rash or irritation develops and lasts.

Keep out of reach of children.

If swallowed, get medical help or contact a Poison Control Center right away.

If pregnant or breast-feeding,

ask a health professional before use

Directions:

- Apply liberally 15 minutes before sun exposure and as needed.
- Children under 6 months of age: ask a doctor.
- Reapply at least every 2 hours
- Use a water-resistant sunscreen if swimming or sweating
- Sun Protection Measures.Spending time in the sun increases your risk of skin cancer and early skin aging. To decrease the risk, regularly use a sunscreen with broad spectrum SPF of 15 or higher and other sun protection measures including:
  -Limit time in the sun, especially between 10 a.m. - 2 p.m.
  -Wear long sleeve shirts, pants, hats and sunglasses.

Other Information:

- Protect this product from excessive heat and direct sunlight.

Inactive Ingredients:

a-Arbutin, Aqua (Deionized Water), Aloe Barbadensis Leaf (Aloe Vera Gel) Juice, Ascorbyl Palmitate (Vitamin C), Azelaic Acid, Bis0VinytlDimethicone/Dimethicone Copolymer, Caprylic/Capric Triglyceride, Cetearyl Alcohol, Cetearyl Glucoside, Cholecalciferol (vitamin D3) Cocos Nucifera (Coconut) Oil, Cucumis Sativus (Cucumber) Extract, Curcuma Longa (Turmeric) Extract, Cyclopentasiloxane, Ethylhexylglycerin, 1- Glutathione, Glycerin, Glyceryl Stearate Citrate, Glycolic Acid, Glycyrrhiza Glabra (Licorice) Extract, Hyaluronic Acid, Hydroxyethyl Acrylate/Sodium Acryloyldimethyl Taurate Copolymer, Magnesium Aluminum Silicate, Morus Alba (Mulberry) Extract, Niacinamide, Phenoxyethanol, Phytonadione (Vitamin K), Polyhydroxystearic Acid, Polysorbate 20, Tocopheryl Acetate (Vitamin E), Zemea (Corn) Propanediol

Questions?

1-888-828-3598